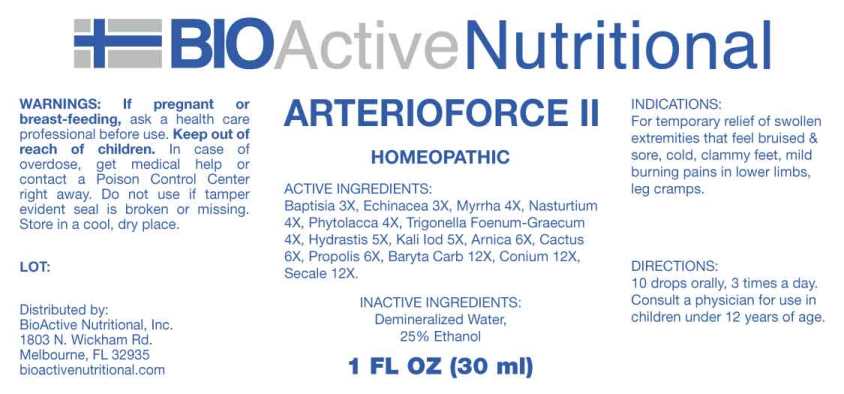 DRUG LABEL: Arterioforce
NDC: 43857-0568 | Form: LIQUID
Manufacturer: BioActive Nutritional, Inc.
Category: homeopathic | Type: HUMAN OTC DRUG LABEL
Date: 20230606

ACTIVE INGREDIENTS: BAPTISIA TINCTORIA ROOT 3 [hp_X]/1 mL; ECHINACEA ANGUSTIFOLIA WHOLE 3 [hp_X]/1 mL; MYRRH 4 [hp_X]/1 mL; NASTURTIUM OFFICINALE 4 [hp_X]/1 mL; PHYTOLACCA AMERICANA ROOT 4 [hp_X]/1 mL; FENUGREEK SEED 4 [hp_X]/1 mL; GOLDENSEAL 5 [hp_X]/1 mL; POTASSIUM IODIDE 5 [hp_X]/1 mL; ARNICA MONTANA WHOLE 6 [hp_X]/1 mL; SELENICEREUS GRANDIFLORUS STEM 6 [hp_X]/1 mL; PROPOLIS WAX 6 [hp_X]/1 mL; BARIUM CARBONATE 12 [hp_X]/1 mL; CONIUM MACULATUM FLOWERING TOP 12 [hp_X]/1 mL; CLAVICEPS PURPUREA SCLEROTIUM 12 [hp_X]/1 mL
INACTIVE INGREDIENTS: WATER; ALCOHOL

DRUG FACTS:

ACTIVE INGREDIENTS:

Baptisia Tinctoria 3X, Echinacea (Angustifolia) 3X, Myrrha 4X, Nasturtium Aquaticum 4X, Phytolacca Decandra 4X, Trigonella Foenum-Graecum 4X, Hydrastis Canadensis 5X, Kali Iodatum 5X, Arnica Montana 6X, Cactus Grandiflorus 6X, Propolis 6X, Baryta Carbonica 12X, Conium Maculatum 12X, Secale Cornutum 12X.

INDICATIONS:

For temporary relief of swollen extremities that feel bruised & sore, cold, clammy feet, mild burning pains in lower limbs, leg cramps.

WARNINGS:

If pregnant or breast-feeding, ask a health care professional before use.

Keep out of reach of children. In case of overdose, get medical help or contact a Poison Control Center right away.

Do not use if tamper evident seal is broken or missing.

Store in cool, dry place.

Keep out of reach of children. In case of overdose, get medical help or contact a Poison Control Center right away.

DIRECTIONS:

10 drops orally, 3 times a day. Consult a physician for use in children under 12 years of age.

INDICATIONS:

For temporary relief of swollen extremities that feel bruised & sore, cold, clammy feet, mild burning pains in lower limbs, leg cramps.

INACTIVE INGREDIENTS:

Demineralized Water, 25% Ethanol

QUESTIONS:

Distributed by:
BioActive Nutritional, Inc.
1803 N. Wickham Rd.
Melbourne, FL 32935
bioactivenutritional.com

PACKAGE LABEL DISPLAY:

BIOActive Nutritional

ARTERIOFORCE II

HOMEOPATHIC

1 FL OZ (30 ml)